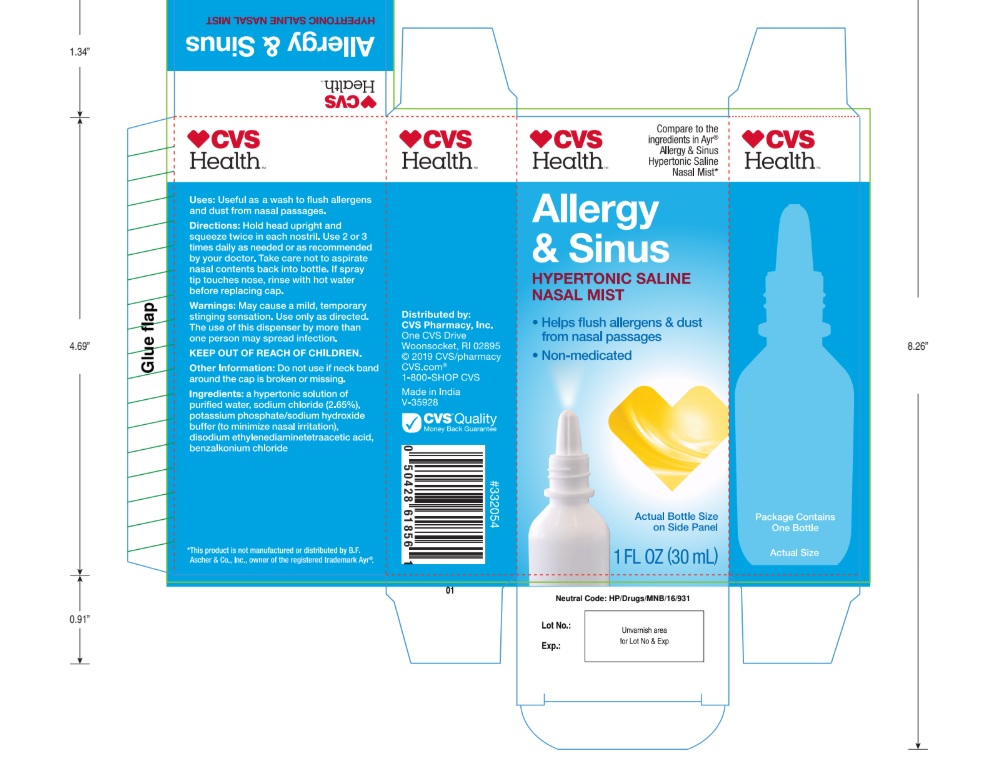 DRUG LABEL: Saline Nasal
NDC: 76168-701 | Form: SPRAY
Manufacturer: Velocity Pharma LLC
Category: otc | Type: HUMAN OTC DRUG LABEL
Date: 20210419

ACTIVE INGREDIENTS: SODIUM CHLORIDE 2.65 mg/100 mL
INACTIVE INGREDIENTS: BENZALKONIUM CHLORIDE; EDETATE DISODIUM ANHYDROUS; WATER

Allergy and Sinus: Hypertonic Saline Mist: CVS Health

Active ingredient

Sodium Chloride, 2.65%

Purpose

Nasal Wash to flush allergens and dust from Nasal Passages

Uses

Nasal congestion
Removes inhaled irritants (dust, dirt, pollen)
Moisturizes dry nasal passages

Warnings

Do not use if seal is broken or missing.

Warnings

Use of this product by more than one person may spread infection
Contents under pressure
Do not puncture or incinerate
Avoid spraying in eyes

Keep out of reach of children. The use of this dispenser by more than one person may spread infection.

Directions

- Squeeze twice in each nostril as needed
- Upright delivers a spray, horizontally a stream, upside down a drop
- Take care not to aspirate nasal contents back into bottle
- If spray tip touches nose, rinse with hot water before replacing cap

Inactive ingredients

A hypertonic solution of purified water, potassium phosphate/Sodium
hydroxide buffer, disodium ethylenediaminetetraacetic acid, benzalkonium chloride